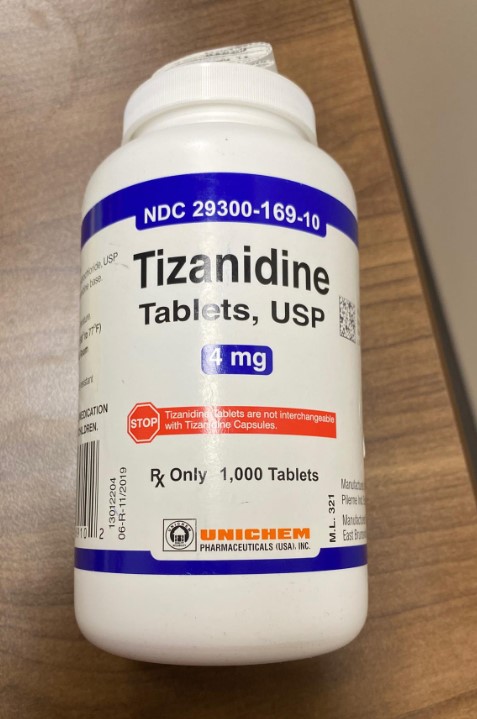 DRUG LABEL: TIZANIDINE
NDC: 80175-0169 | Form: TABLET
Manufacturer: Central Packaging
Category: prescription | Type: HUMAN PRESCRIPTION DRUG LABEL
Date: 20210218

ACTIVE INGREDIENTS: TIZANIDINE HYDROCHLORIDE 4 mg/1 1

INDICATIONS AND USAGE

Tizanidine is a central alpha-2-adrenergic agonist indicated for the management of spasticity. Because of the short duration of therapeutic effect, treatment with tizanidine should be reserved for those daily activities and times when relief of spasticity is most important.